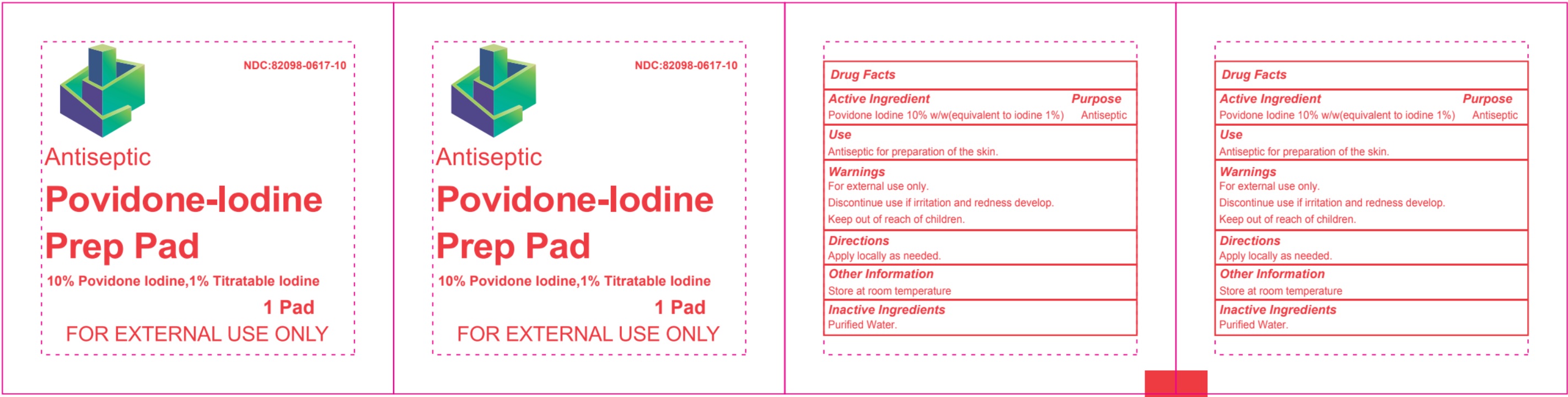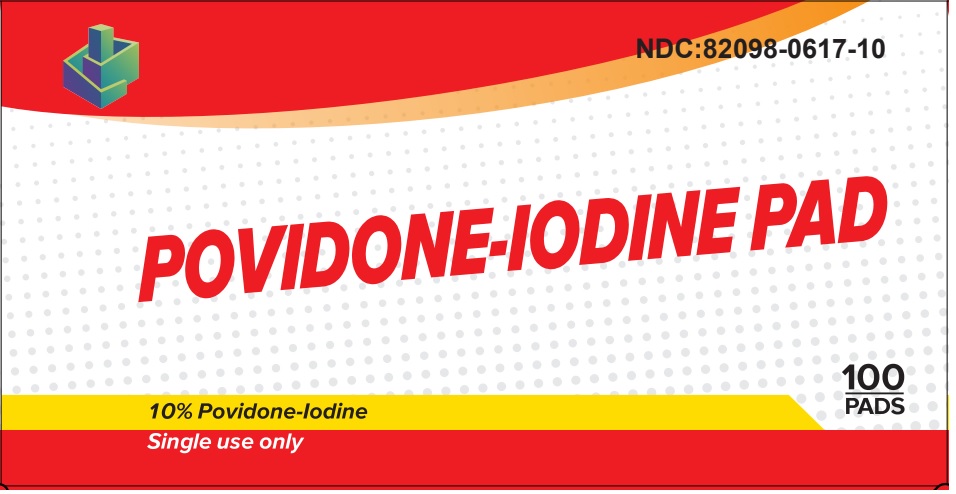 DRUG LABEL: POVIDONE-IODINE PAD- povidone-iodine swab
NDC: 82098-617 | Form: SWAB
Manufacturer: Raya Pharmaceuticals LLC
Category: otc | Type: HUMAN OTC DRUG LABEL
Date: 20231027

ACTIVE INGREDIENTS: POVIDONE-IODINE 10 g/100 g
INACTIVE INGREDIENTS: WATER

POVIDONE-IODINE PAD
10% POVIDONE-IODINE

INDICATIONS AND USAGE

Antiseptic for preparation of the skin.

For external use only.

Apply locally as needed.

PRECAUTIONS

For external use only.

WARNINGS AND PRECAUTIONS

For external use only.

Discontinue use if irritation and redness develop.

Keep out of reach of children.

STORAGE AND HANDLING

Store at room temperature

DOSAGE AND ADMINISTRATION

Apply Localy As Needed

WARNINGS

For External Use Only

Discontinue use if Irretation and reddness appear

Keep Out of Reach of Children

Water is added as inactive ingredient

ACTIVE INGREDIENT

POVIDONE-IODINE 10% W/W(equivelent to iodine 1%)

PURPOSE

POVIDONE-IODINE 10% W/W(equivelent to iodine 1%)................. Purpose: Antiseptic

Keep Out of reach of Children

PACKAGE LABEL

NDC:82098-0617-10

POVIDONE-IODINE PAD

10% POVIDONE-IODINE

Single USE Only